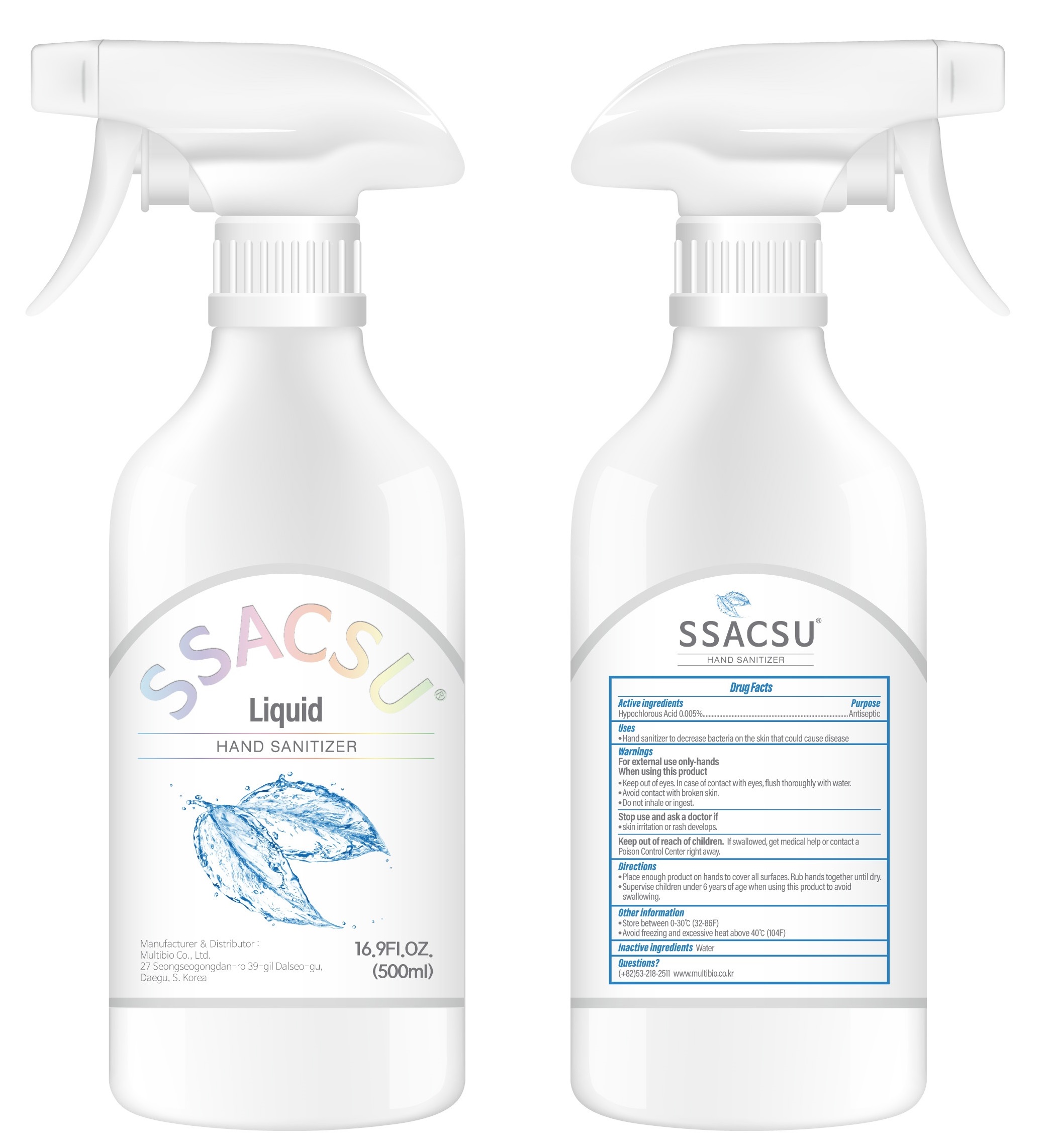 DRUG LABEL: SSACSU Hand sanitizer
NDC: 76847-011 | Form: SPRAY
Manufacturer: Multibio Co., Ltd.
Category: otc | Type: HUMAN OTC DRUG LABEL
Date: 20200511

ACTIVE INGREDIENTS: Hypochlorous Acid 0.025 g/500 mL
INACTIVE INGREDIENTS: Water

ACTIVE INGREDIENT

Active ingredients: Hypochlorous Acid 0.005%

INACTIVE INGREDIENT

Inactive ingredients
Water

PURPOSE

Purpose: Antiseptic

WARNINGS

For external use only-hands

When using this product
■ Keep out of eyes. In case of contact with eyes, flush thoroughly with water. ■ Avoid contact with broken skin. ■ Do not inhale or ingest.

Stop use and ask a doctor if skin irritation or rash develops.

KEEP OUT OF REACH OF CHILDREN

If swallowed, get medical help or contact a Poison Control Center right away.

Uses

Hand sanitizer to decrease bacteria on the skin that could cause disease

Directions

Place enough product on hands to cover all surfaces. Rub hands together until dry.
Supervise children under 6 years of age when using this product to avoid swallowing.

Other information

Store between 0-30C (32-86F)
Avoid freezing and excessive heat above 40C (104F)

QUESTIONS

053-218-2511 www.multibio.co.kr